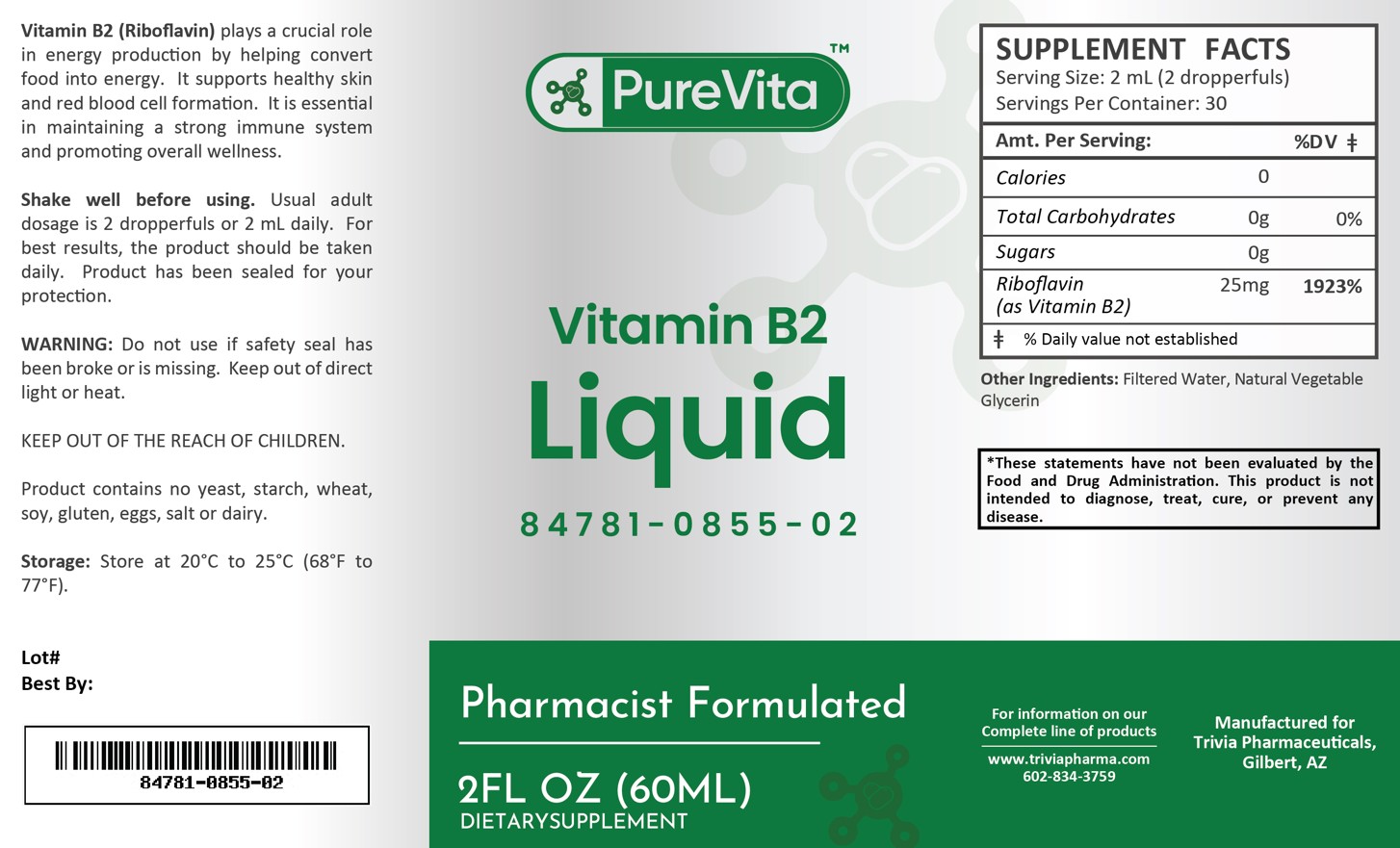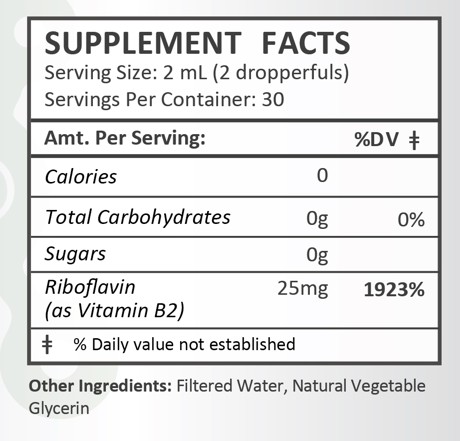 DRUG LABEL: PureVita Vitamin B2
NDC: 84781-855 | Form: LIQUID
Manufacturer: Trivia Pharmaceuticals, LLC
Category: other | Type: Dietary Supplement
Date: 20250306

ACTIVE INGREDIENTS: RIBOFLAVIN 25 mg/2 mL

PureVita Vitamin B2

Health Claim:

PureVita Vitamin B2

Description:

Vitamin B2 (Riboflavin) plays a crucial role in energy production by helping convert food into energy. It supports healthy skin and red blood cell formation. It is essential in maintaining a strong immune system and promoting overall wellness.

This listed product is not a National Drug Code, but instead has merely been formatted to comply with standard industry practice for pharmacy and insurance computer systems.

Warnings:

Do not use if safety seal has been broken or is missing. Keep out of direct light or heat.

KEEP OUT OF THE REACH OF CHILDREN.

Product contains no yeast, starch, wheat, soy, gluten, eggs, salt or dairy.

Dosage and Administration:

Usual adult dose is 2 dropperfuls or 2 mL daily. For the best results, the product should be taken daily. Product has been sealed for your protection.

How Supplied:

PureVita Vitamin B2 Liquid is supplied as white, clear liquid.

84781-0855-02

Reserved for Professional Recommendation: All prescriptions using this product shall be pursuant to state statutes as applicable. This is not an Orange Book product. There are no implied or explicit claims on therapeutic equivalence.

Manufactured for:

Trivia Pharmaceuticals

Gilbert, AZ

Storage:

Storage: Store at 20oC to 25oC (68oF to 77oF). Keep refrigerated after opening.